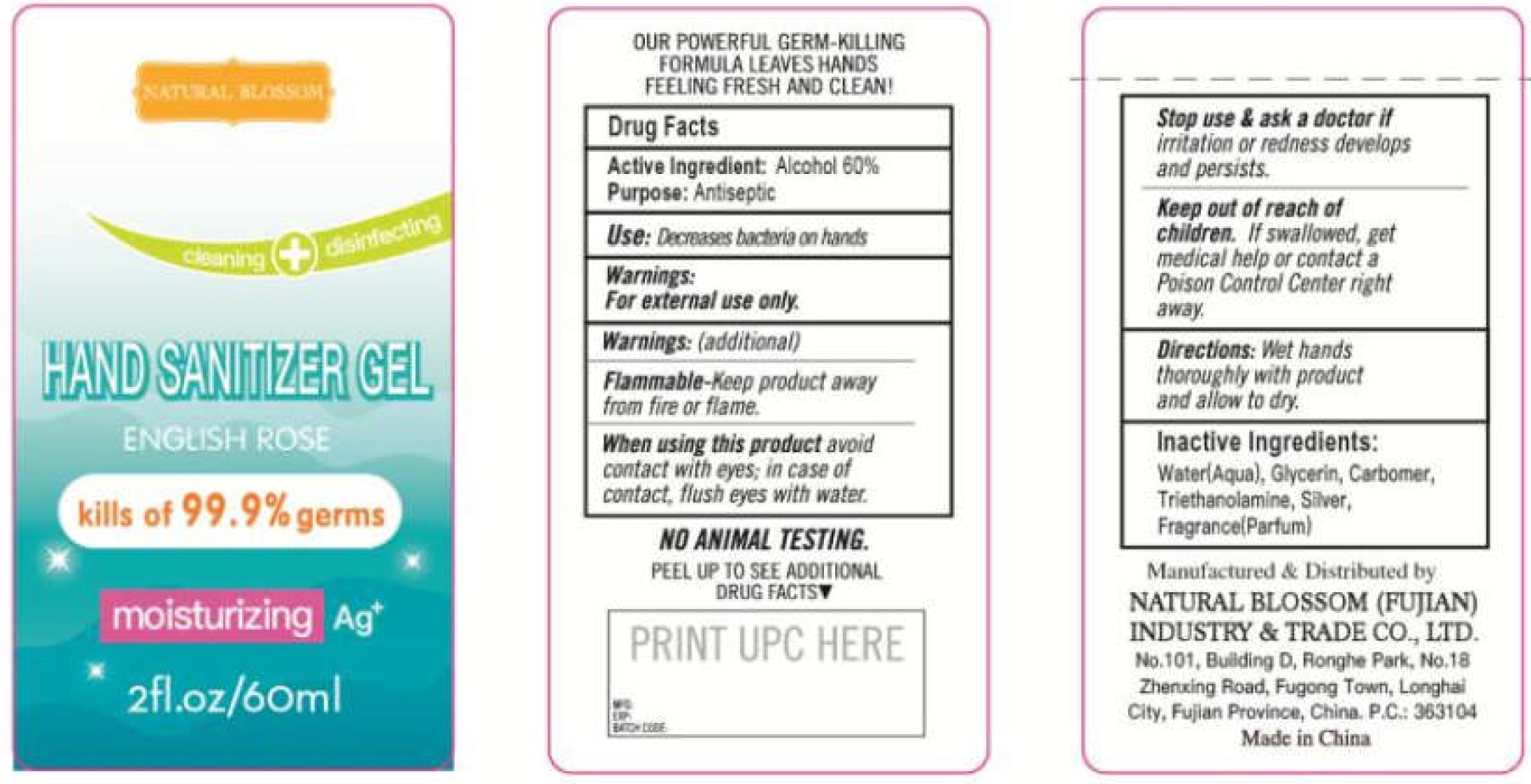 DRUG LABEL: Hand Sanitizer
NDC: 74711-001 | Form: GEL
Manufacturer: Natural Blossom (Fujian) Industry & Trade Co., Ltd.
Category: otc | Type: HUMAN OTC DRUG LABEL
Date: 20200416

ACTIVE INGREDIENTS: ALCOHOL 0.6 mL/1 mL
INACTIVE INGREDIENTS: WATER; GLYCERIN; CARBOMER HOMOPOLYMER, UNSPECIFIED TYPE; TROLAMINE; SILVER

Hand Sanitizer Gel

Active Ingredient

Alcohol 60%

Purpose:

Antiseptic

Use:

Decreases bacteria on hands

Warnings:

For external use only.

Warnings: (additional)

Flammable-Keep product away from fire or flame.

When using this product

avoid contact with eyes; in case of contact, flush eyes with water.

Stop use & ask a doctor if

irritation or redness develops and persists.

Keep out or reach of children.

If swallowed, get medical help or contact a Poison Control Center right away.

Directions:

Wet hands thoroughly with product and allow to dry.

Inactive Ingredients:

Water(Aqua), Glycerin, Carbomer, Triethanolamine, Siliver, Fragrance(Parfum)